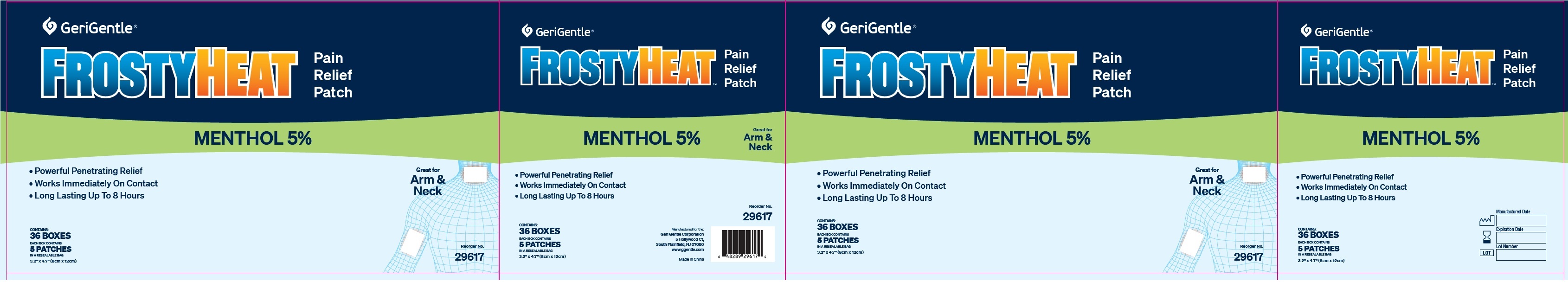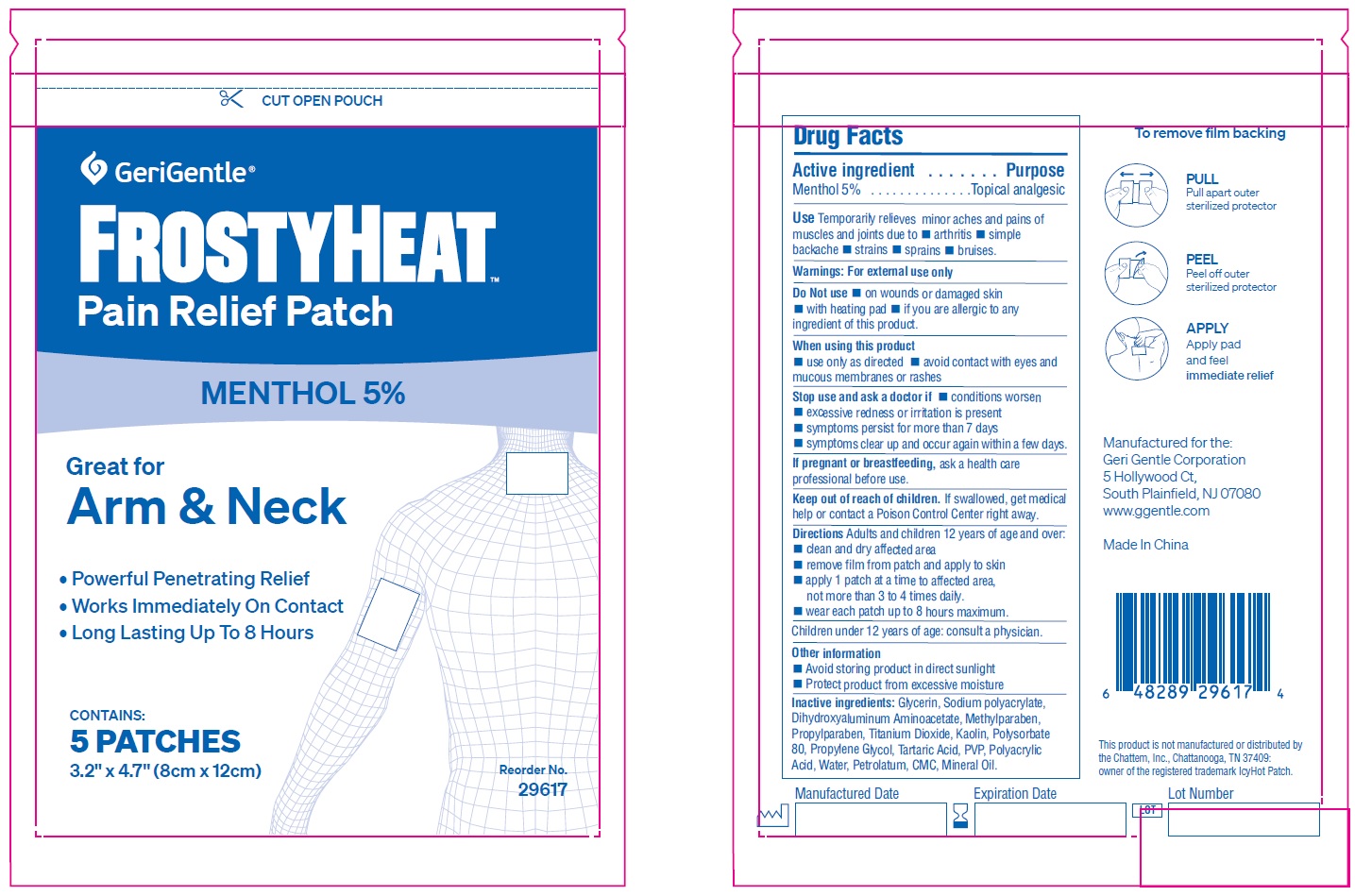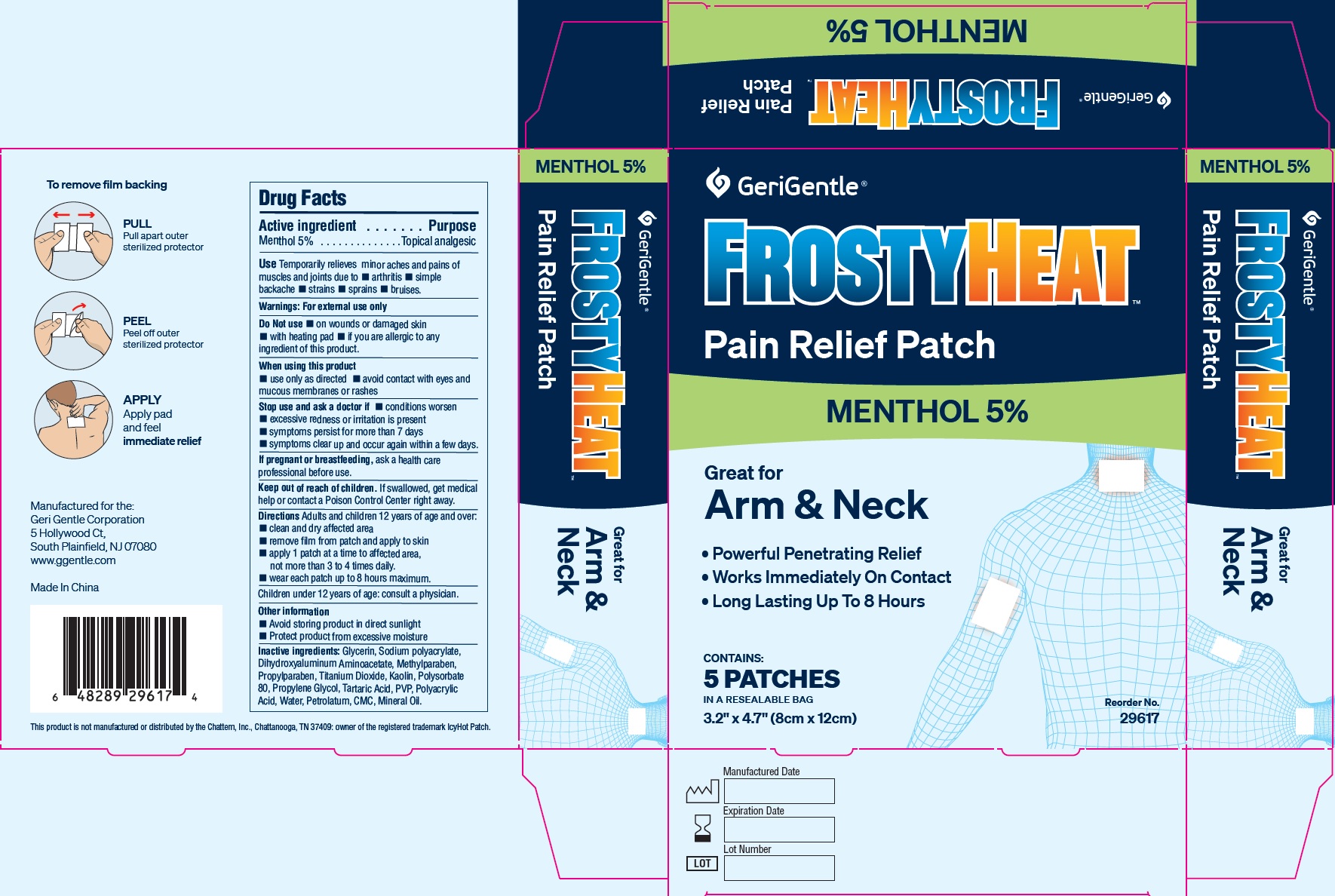 DRUG LABEL: GeriGentle FrostyHeat Pain Relief Patch Arm and Neck
NDC: 69771-011 | Form: PATCH
Manufacturer: Geri-Gentle Corporation
Category: otc | Type: HUMAN OTC DRUG LABEL
Date: 20231110

ACTIVE INGREDIENTS: MENTHOL 50 mg/1 mL
INACTIVE INGREDIENTS: GLYCERIN; DIHYDROXYALUMINUM AMINOACETATE; METHYLPARABEN; PROPYLPARABEN; TITANIUM DIOXIDE; KAOLIN; POLYSORBATE 80; PROPYLENE GLYCOL; TARTARIC ACID; POVIDONE, UNSPECIFIED; WATER; PETROLATUM; CARBOXYMETHYLCELLULOSE SODIUM, UNSPECIFIED; MINERAL OIL

GeriGentle FrostyHeat Pain Relief Patch Arm and Neck

Active ingredient

Menthol 5%

Purpose

Topical anesthetic

Use

- Temporarily relieves minor aches and pains of muscles and joints due to
- arthritis
- simple backache
- strains
- sprains
- bruises.

Warnings:

For external use only

Do not use

- on wounds or damaged skin
- with heating pad
- if you are allergic to any ingredient of this product.

When using this product

- use only as directed
- avoid contact with eyes and mucous membranes or rashes

Stop use and ask a doctor if

- conditions worsen
- excessive redness or irritation is present
- symptoms persist for more than 7 days
- symptoms clear up and occur again within a few days.

If pregnant or breast-feeding,

ask a health care professional before use.

Keep out of reach of children and pets.

If swallowed, get medical help or contact a Poison Control Center right away.

Directions:

Adults and children 12 years of age and over:Clean and dry affected area.

Children under 12 years of age: consult a physician.

- clean and dry affected area
- remove film from patch and apply to skin
- apply 1 patch at a time to affected area, not more than 3 to 4 times daily.
- wear each patch up to 8 hours maximum.

Other information:

- Avoid storing product in direct sunlight
- Protect product from excessive moisture

Inactive ingredients:

Glycerin, Sodium polyacrylate, Dihydroxyaluminum Aminoacetate, Methylparaben, Propylparaben, Titanium Dioxide, Kaolin, Polysorbate 80, Propylene Glycol, Tartaric Acid, PVP, Polyacrylic Acid, Water, Petrolatum, CMC, Mineral Oil.